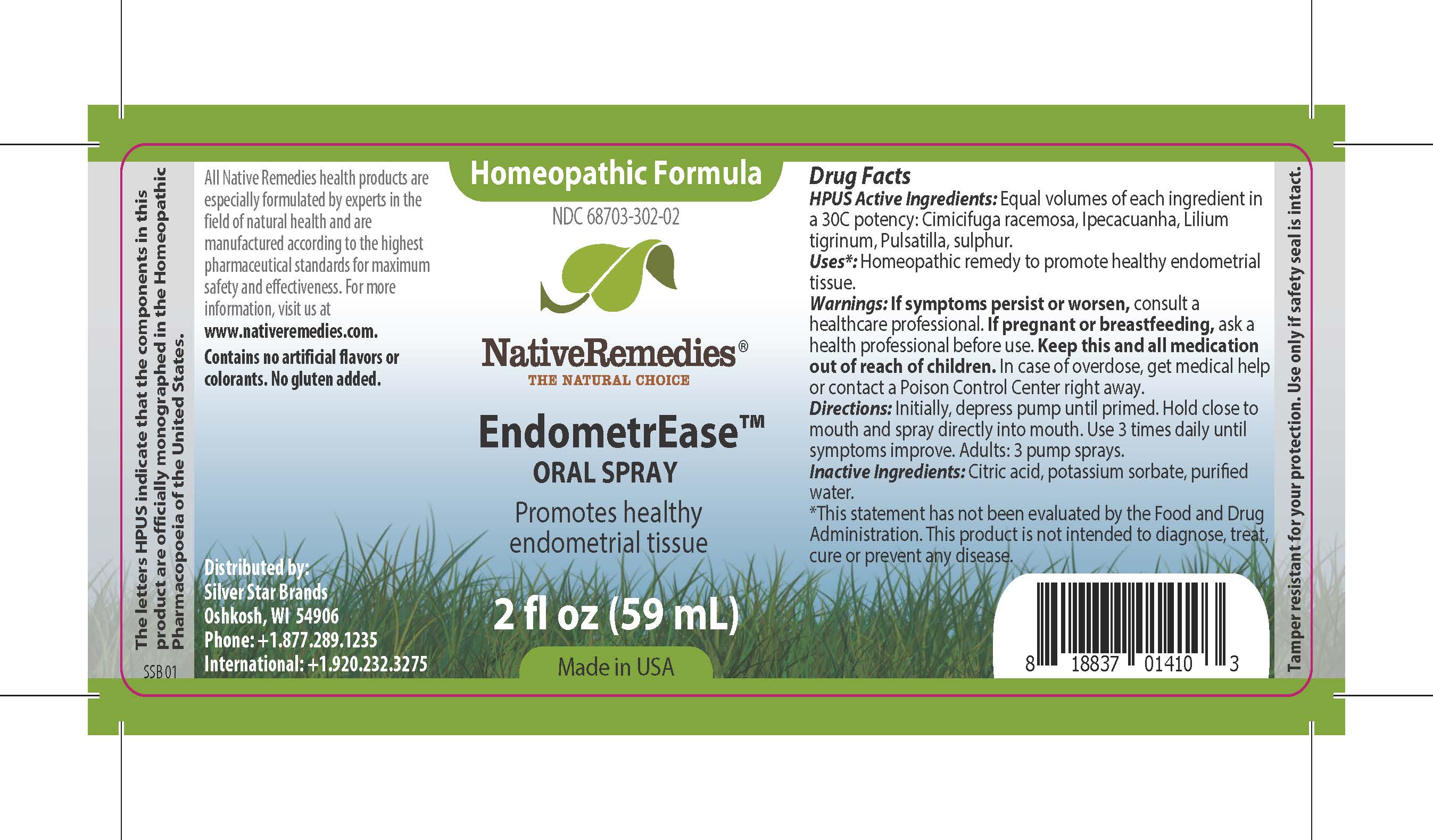 DRUG LABEL: EndometrEase
NDC: 68703-302 | Form: SPRAY
Manufacturer: Silver Star Brands
Category: homeopathic | Type: HUMAN OTC DRUG LABEL
Date: 20241202

ACTIVE INGREDIENTS: BLACK COHOSH 30 [hp_C]/59 mL; LILIUM LANCIFOLIUM WHOLE FLOWERING 30 [hp_C]/59 mL; ANEMONE PULSATILLA 30 [hp_C]/59 mL; IPECAC 30 [hp_C]/59 mL; SULFUR 30 [hp_C]/59 mL
INACTIVE INGREDIENTS: ANHYDROUS CITRIC ACID; WATER; POTASSIUM SORBATE

NativeRemedies® EndomtrEase™ Oral Spray

HPUS Active Ingredients:

Equal volumes of each ingredient in a 30C potency: Cimicifuga racemosa, Ipecacuanha, Lilium tigrinum, Pulsatilla, Sulphur.

Uses*:

Homeopathic remedy to promote healthy endometrial tissue.

*This statement has not been evaluated by the Food and Drug Administration. This product is not intended to diagnose, treat, cure or prevent any disease.

Warnings:

If symptoms persist or worsen, consult a healthcare professional. If pregnant or breastfeeding, ask a health professional before use. Keep this and all medication out of reach of children. In case of overdose, get medical help or contact a Poison Control Center right away.

Directions:

Initially, depress pump until primed. Hold close to mouth and spray directly into mouth. Use 3 times daily until symptoms improve. Adults: 3 pump sprays.

OTHER SAFETY INFORMATION

All Native Remedies health products are especially formulated by experts in the field of natural health and are manufactured according to the highest pharmaceutical standards for maximum safety and effectiveness. For more information, visit us at www.nativeremedies.com.

Contains no artificial flavors or colorants. No gluten added.

Inactive Ingredients:

Citric acid, potassium sorbate, purified water.

KEEP OUT OF REACH OF CHILDREN

Keep this and all medication out of reach of children. In case of overdose, get medical help or contact a Poison Control Center right away.

PREGNANCY OR BREAST FEEDING

If pregnant or breastfeeding, ask a health professional before use.

PURPOSE

Promotes healthy endometrial tissue